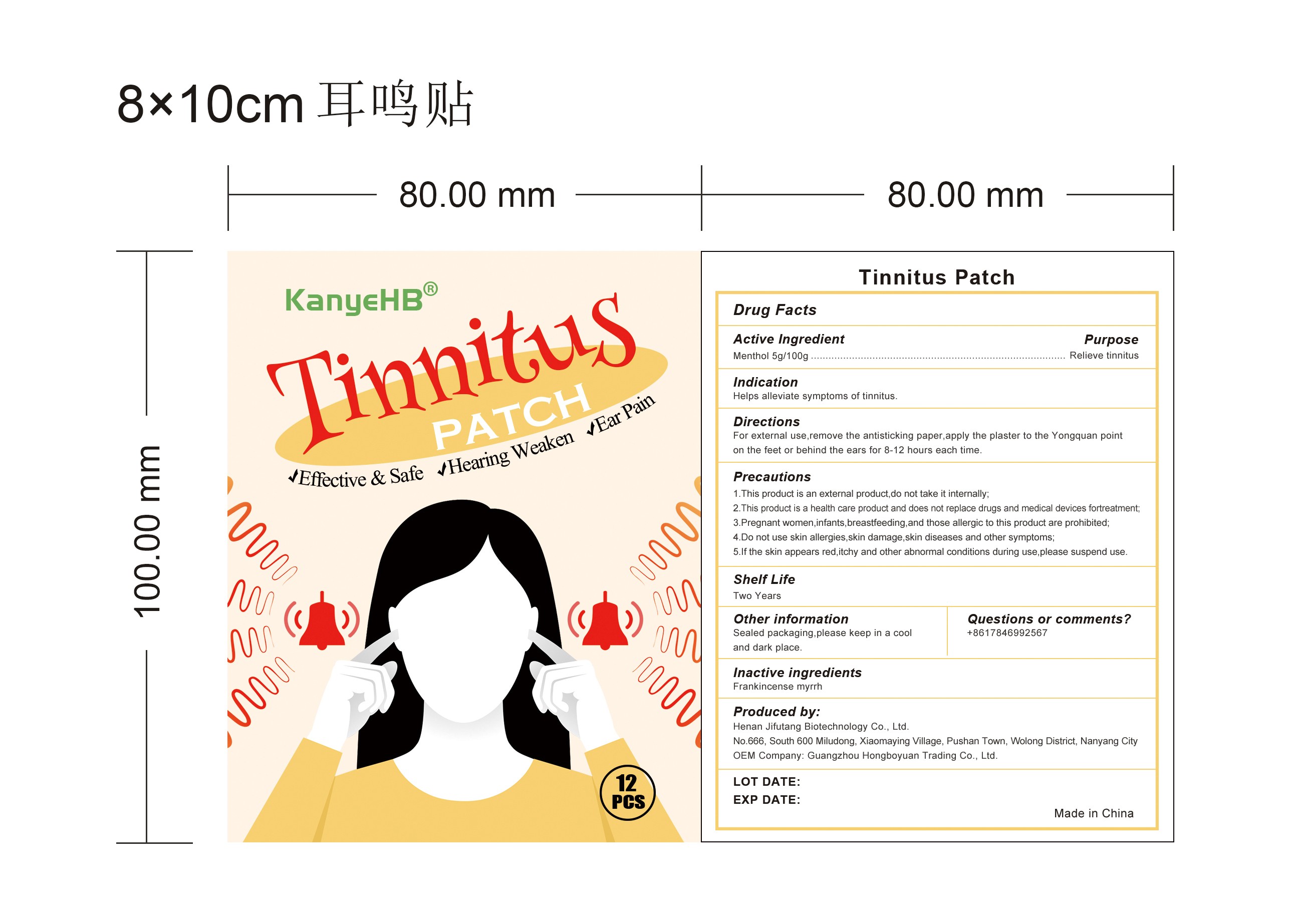 DRUG LABEL: Tinnitus Patch
NDC: 83713-006 | Form: PATCH
Manufacturer: Guangzhou Hongboyuan Trading Co., Ltd.
Category: otc | Type: HUMAN OTC DRUG LABEL
Date: 20231017

ACTIVE INGREDIENTS: MENTHOL 5 g/100 g
INACTIVE INGREDIENTS: MYRRH; FRANKINCENSE

Tinnitus Patch 83713-006-22

Active ingredient: Menthol 5g/100g

Purpose: Relieve tinnitus

INDICATIONS AND USAGE

Use to: Helps alleviate symptoms of tinnitus

DOSAGE AND ADMINISTRATION

Directions: For external use,remove the antisticking paper,apply the plaster to the Yongquan point on the feet or behind the ears for 8-12 hours each time

WARNINGS

Precautions

1. This product is an external product,do not take it internally;

2. This product is a disposable external product,not a substitute for drugs or medical equipment;Do not reuse it;

3. Pregnant women,infants,breastfeeding,and those allergic to this product are prohibited;

4. Do not use skin allergies,skin damage,skin diseases and other symptoms;

5. If the skin appears red,itchy and other abnormal conditions during use,please suspend use.

Questions or comments? +8617846992567

Inactive Ingredients: Frankincense, myrrh

Other information: Sealed packaging.please keep in a cool and dark place

Produced by:Henan Jifutang Biotechnology Co., Ltd.

No.666,South 600 Miludong,Xiaomaying Village,Pushan Town,Wolong District,Nanyang City

OEM Company: Guangzhou Hongboyuan Trading Co., Ltd.

Made in China

KEEP OUT OF REACH OF CHILDREN

Same as WARNINGS SECTION

see label